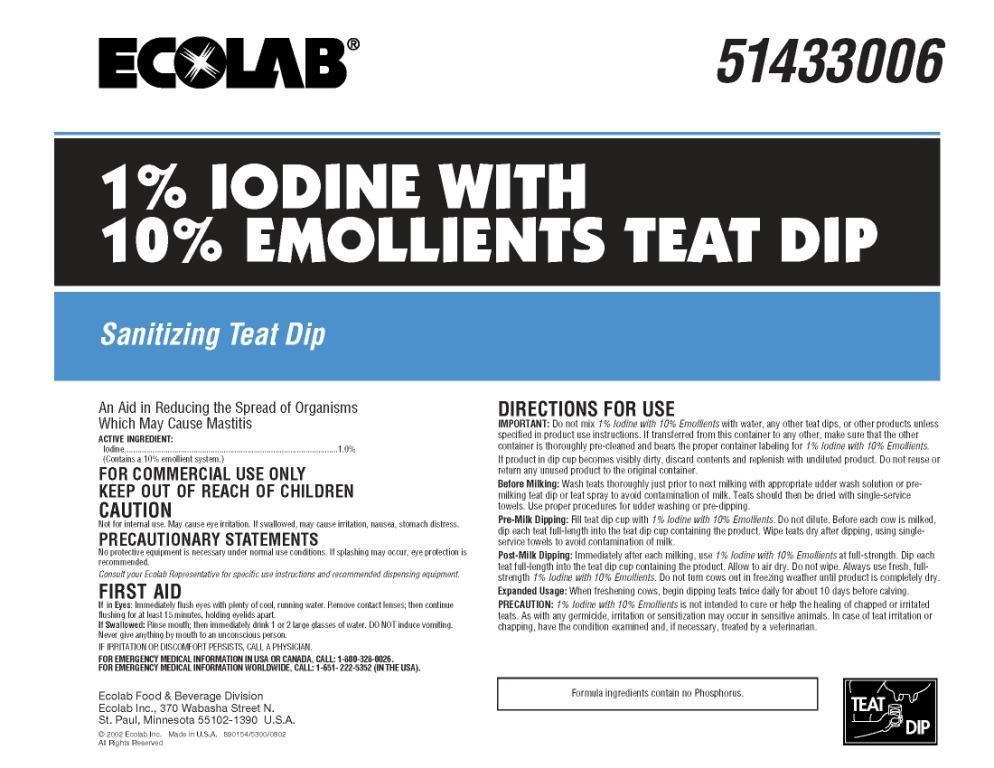 DRUG LABEL: Ecolab
NDC: 47593-396 | Form: SOLUTION
Manufacturer: Ecolab Inc.
Category: animal | Type: OTC ANIMAL DRUG LABEL
Date: 20201215

ACTIVE INGREDIENTS: IODINE 10.65 mg/1 mL
INACTIVE INGREDIENTS: GLYCERIN; SORBITOL; WATER

GENERAL PRECAUTIONS

FOR COMMERCIAL USE ONLY
KEEP OUT OF REACH OF CHILDREN

WARNINGS AND PRECAUTIONS

CAUTION
Not for internal use. May cause eye irritation. If swallowed, may cause irritation, nausea, stomach distress.
PRECAUTIONARY STATEMENTS
No protective equipment is necessary under normal use conditions. If splashing may occur, eye protection is
recommended.
Consult your Ecolab Representative for specific use instructions and recommended dispensing equipment.

SAFE HANDLING WARNING

FIRST AID
If in Eyes: Immediately flush eyes with plenty of cool, running water. Remove contact lenses; then continue
flushing for at least 15 minutes, holding eyelids apart.
If Swallowed: Rinse mouth; then immediately drink 1 or 2 large glasses of water. DO NOT induce vomiting.
Never give anything by mouth to an unconscious person.
IF IRRITATION OR DISCOMFORT PERSISTS, CALL A PHYSICIAN.
FOR EMERGENCY MEDICAL INFORMATION IN USA OR CANADA, CALL: 1-800-328-0026.
FOR EMERGENCY MEDICAL INFORMATION WORLDWIDE, CALL: 1-651- 222-5352 (IN THE USA).

VETERINARY INDICATIONS

DIRECTIONS FOR USE
IMPORTANT: Do not mix 1% Iodine with 10% Emollients with water, any other teat dips, or other products unless
specified in product use instructions. If transferred from this container to any other, make sure that the other
container is thoroughly pre-cleaned and bears the proper container labeling for 1% Iodine with 10% Emollients.
If product in dip cup becomes visibly dirty, discard contents and replenish with undiluted product. Do not reuse or
return any unused product to the original container.
Before Milking: Wash teats thoroughly just prior to next milking with appropriate udder wash solution or premilking
teat dip or teat spray to avoid contamination of milk. Teats should then be dried with single-service
towels. Use proper procedures for udder washing or pre-dipping.
Pre-Milk Dipping: Fill teat dip cup with 1% Iodine with 10% Emollients. Do not dilute. Before each cow is milked,
dip each teat full-length into the teat dip cup containing the product. Wipe teats dry after dipping, using singleservice
towels to avoid contamination of milk.
Post-Milk Dipping: Immediately after each milking, use 1% Iodine with 10% Emollients at full-strength. Dip each
teat full-length into the teat dip cup containing the product. Allow to air dry. Do not wipe. Always use fresh, fullstrength
1% Iodine with 10% Emollients. Do not turn cows out in freezing weather until product is completely dry.
Expanded Usage: When freshening cows, begin dipping teats twice daily for about 10 days before calving.
PRECAUTION:1% Iodine with 10% Emollients is not intended to cure or help the healing of chapped or irritated
teats. As with any germicide, irritation or sensitization may occur in sensitive animals. In case of teat irritation or
chapping, have the condition examined and, if necessary, treated by a veterinarian.

Principal Display Panel and Representative Label

ECOLAB 51433006

1% IODINE WITH
10% EMOLLIENTS TEAT DIP

Sanitizing Teat Dip

An Aid in Reducing the Spread of Organisms
Which May Cause Mastitis

ACTIVE INGREDIENT:
Iodine...................................................................................................1.0%
(Contains a 10% emollient system.)

Ecolab Food and Beverage Division
Ecolab Inc., 370 Wabasha Street N.
St. Paul, Minnesota 55102-1390 U.S.A.
© 2002 Ecolab Inc. Made in U.S.A. 890154/5300/0802
All Rights Reserved